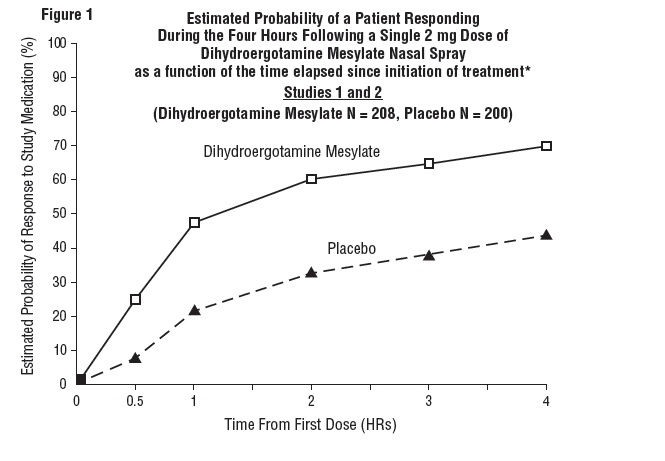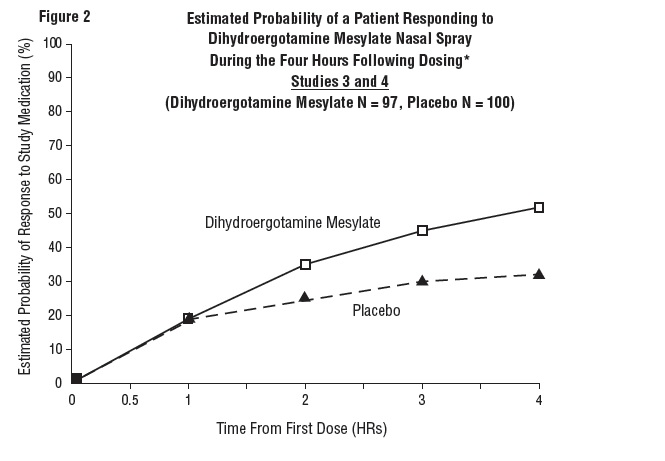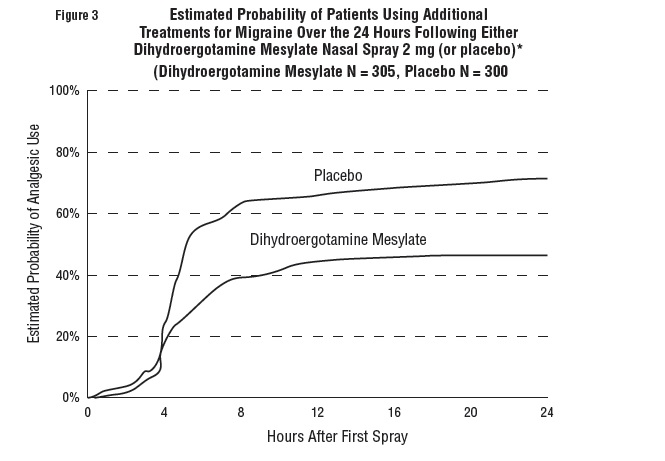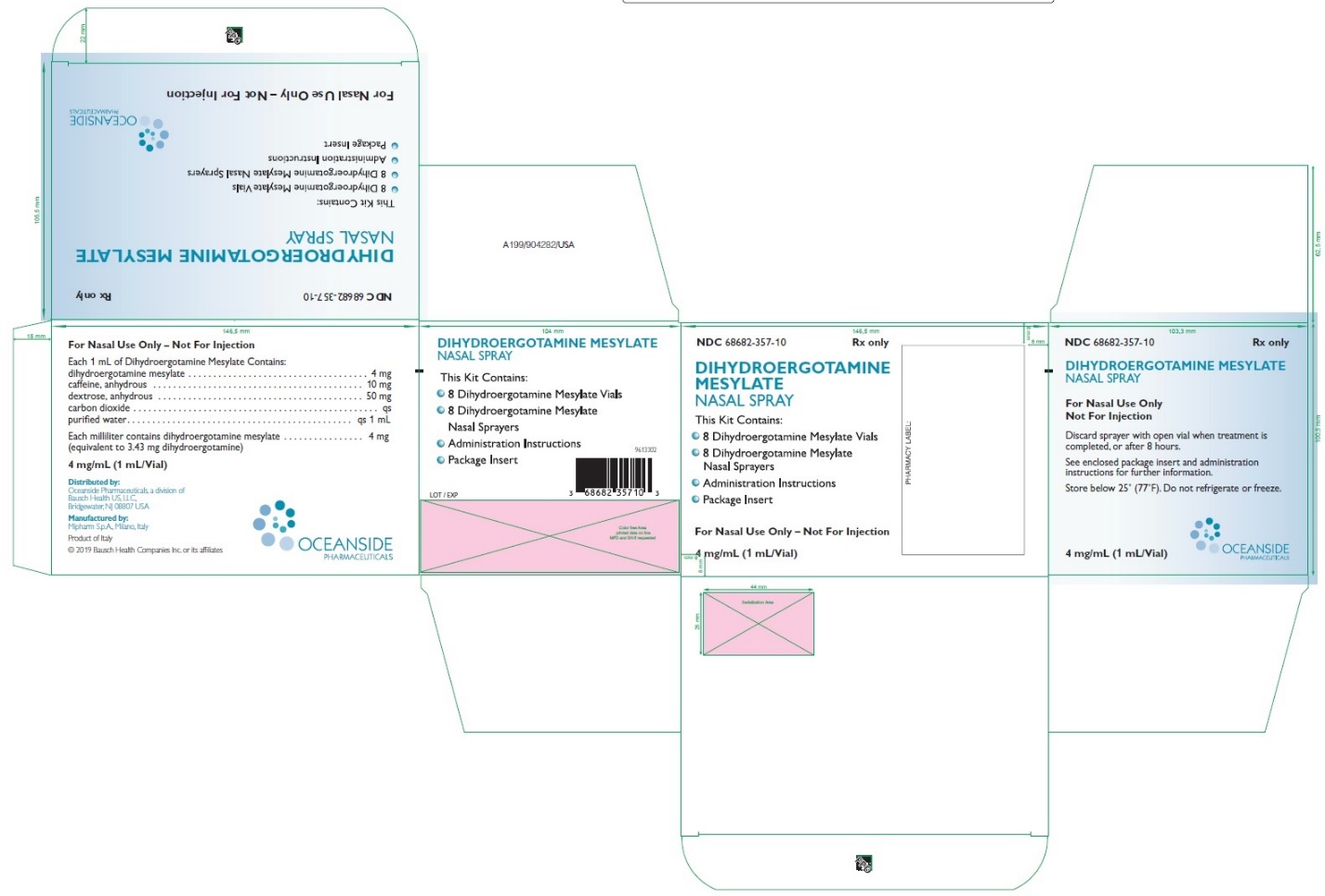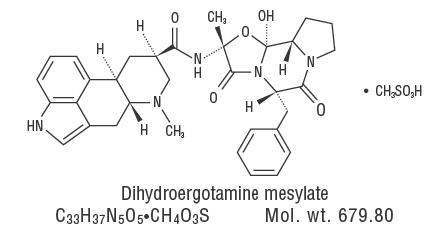 DRUG LABEL: Dihydroergotamine Mesylate
NDC: 68682-357 | Form: SPRAY
Manufacturer: Oceanside Pharmaceuticals
Category: prescription | Type: HUMAN PRESCRIPTION DRUG LABEL
Date: 20250306

ACTIVE INGREDIENTS: DIHYDROERGOTAMINE MESYLATE 4 mg/1 mL
INACTIVE INGREDIENTS: CAFFEINE; ANHYDROUS DEXTROSE; CARBON DIOXIDE; WATER

Dihydroergotamine Mesylate
Nasal Spray

The solution used in Dihydroergotamine Mesylate Nasal Spray (4 mg/mL) is intended for intranasal use and must not be injected.

Rx Only

WARNING: PERIPHERAL ISCHEMIA FOLLOWING COADMINISTRATION WITH POTENT CYP3A4 INHIBITORS

Serious and/or life-threatening peripheral ischemia has been associated with the coadministration of DIHYDROERGOTAMINE with potent CYP 3A4 inhibitors including protease inhibitors and macrolide antibiotics. Because CYP 3A4 inhibition elevates the serum levels of DIHYDROERGOTAMINE, the risk for vasospasm leading to cerebral ischemia and/or ischemia of the extremities is increased. Hence, concomitant use of these medications is contraindicated.

(see CONTRAINDICATIONSand WARNINGS).

DESCRIPTION

Dihydroergotamine mesylate is ergotamine hydrogenated in the 9,10 position as the mesylate salt. Dihydroergotamine Mesylate Nasal Spray is known chemically as ergotaman-3’, 6’, 18-trione, 9,10-dihydro-12’-hydroxy-2’-methyl-5’- (phenylmethyl)-, (5’α)-, monomethane-sulfonate. Its molecular weight is 679.78 and its empirical formula is C33H37N5O5•CH4O3S.

The chemical structure is:

Dihydroergotamine Mesylate Nasal Spray is provided for intranasal administration as a clear, colorless to light yellow aqueous solution in an amber glass vial containing:

dihydroergotamine mesylate | 4 mg
caffeine, anhydrous | 10 mg
dextrose, anhydrous | 50 mg
carbon dioxide | qs
purified water | qs 1 mL
Each milliliter contains
Dihydroergotamine mesylate | 4 mg
(equivalent to 3.43 mg dihydroergotamine)

CLINICAL PHARMACOLOGY

Mechanism of Action

Dihydroergotamine binds with high affinity to 5-HT1Dαand 5-HT1Dβreceptors. It also binds with high affinity to serotonin 5-HT1A, 5-HT2A, and 5-HT2Creceptors, noradrenaline α2A, α2Band α1receptors, and dopamine D2Land D3receptors.

The therapeutic activity of dihydroergotamine in migraine is generally attributed to the agonist effect at 5-HT1Dreceptors. Two current theories have been proposed to explain the efficacy of 5-HT1Dreceptor agonists in migraine. One theory suggests that activation of 5-HT1Dreceptors located on intracranial blood vessels, including those on arterio-venous anastomoses, leads to vasoconstriction, which correlates with the relief of migraine headache. The alternative hypothesis suggests that activation of 5-HT1Dreceptors on sensory nerve endings of the trigeminal system results in the inhibition of pro-inflammatory neuropeptide release. In addition, dihydroergotamine possesses oxytocic properties.

Pharmacokinetics

Absorption

Dihydroergotamine mesylate is poorly bioavailable following oral administration. Following intranasal administration, however, the mean bioavailability of dihydroergotamine mesylate is 32% relative to the injectable administration. Absorption is variable, probably reflecting both intersubject differences of absorption and the technique used for self-administration.

Distribution

Dihydroergotamine mesylate is 93% plasma protein bound. The apparent steady-state volume of distribution is approximately 800 liters.

Metabolism

Four dihydroergotamine mesylate metabolites have been identified in human plasma following oral administration. The major metabolite, 8’-β-hydroxydihydroergotamine, exhibits affinity equivalent to its parent for adrenergic and 5-HT receptors and demonstrates equivalent potency in several venoconstrictor activity models, in vivoand in vitro. The other metabolites, i.e., dihydrolysergic acid, dihydrolysergic amide and a metabolite formed by oxidative opening of the proline ring are of minor importance. Following nasal administration, total metabolites represent only 20%-30% of plasma AUC. The systemic clearance of dihydroergotamine mesylate following I.V. and I.M. administration is 1.5 L/min. Quantitative pharmacokinetic characterization of the four metabolites has not been performed.

Excretion

The major excretory route of dihydroergotamine is via the bile in the feces. After intranasal administration the urinary recovery of parent drug amounts to about 2% of the administered dose compared to 6% after I.M. administration. The total body clearance is 1.5 L/min which reflects mainly hepatic clearance. The renal clearance (0.1 L/min) is unaffected by the route of dihydroergotamine administration. The decline of plasma dihydroergotamine is biphasic with a terminal half-life of about 10 hours.

Subpopulations

No studies have been conducted on the effect of renal or hepatic impairment, gender, race, or ethnicity on dihydroergotamine pharmacokinetics. Dihydroergotamine Mesylate Nasal Spray is contraindicated in patients with severely impaired hepatic or renal function (see CONTRAINDICATIONS).

Interactions

The pharmacokinetics of dihydroergotamine did not appear to be significantly affected by the concomitant use of a local vasoconstrictor (e.g., fenoxazoline).

Multiple oral doses of the β-adrenoceptor antagonist propranolol, used for migraine prophylaxis, had no significant influence on the Cmax, Tmax or AUC of dihydroergotamine doses up to 4 mg. Pharmacokinetic interactions have been reported in patients treated orally with other ergot alkaloids (e.g., increased levels of ergotamine) and macrolide antibiotics, principally troleandomycin, presumably due to inhibition of cytochrome P450 3A metabolism of the alkaloids by troleandomycin. Dihydroergotamine has also been shown to be an inhibitor of cytochrome P450 3A catalyzed reactions and rare reports of ergotism have been obtained from patients treated with dihydroergotamine and macrolide antibiotics (e.g., troleandomycin, clarithromycin, erythromycin), and in patients treated with dihydroergotamine and protease inhibitors (e.g. ritonavir), presumably due to inhibition of cytochrome P450 3A metabolism of ergotamine (see CONTRAINDICATIONS). No pharmacokinetic interactions involving other cytochrome P450 isoenzymes are known.

Clinical Trials

The efficacy of Dihydroergotamine Mesylate Nasal Spray for the acute treatment of migraine headaches was evaluated in four randomized, double-blind, placebo-controlled studies in the U.S. The patient population for the trials was predominantly female (87%) and Caucasian (95%) with a mean age of 39 years (range 18 to 65 years). Patients treated a single moderate to severe migraine headache with a single dose of study medication and assessed pain severity over the 24 hours following treatment. Headache response was determined 0.5, 1, 2, 3 and 4 hours after dosing and was defined as a reduction in headache severity to mild or no pain. In studies 1 and 2, a four-point pain intensity scale was utilized; in studies 3 and 4, a five-point scale was used that included both pain response and restoration of function for “severe” or “incapacitating” pain, a less clear endpoint. Although rescue medication was allowed in all four studies, patients were instructed not to use them during the four-hour observation period. In studies 3 and 4, a total dose of 2 mg was compared to placebo. In studies 1 and 2, doses of 2 and 3 mg were evaluated, and showed no advantage of the higher dose for a single treatment. In all studies, patients received a regimen consisting of 0.5 mg in each nostril, repeated in 15 minutes (and again in another 15 minutes for the 3 mg dose in studies 1 and 2).

The percentage of patients achieving headache response 4 hours after treatment was significantly greater in patients receiving 2 mg doses of Dihydroergotamine Mesylate Nasal Spray compared to those receiving placebo in 3 of the 4 studies (see Tables 1 & 2 and Figures 1 & 2).

Table 1: Studies 1 and 2: Percentage of Patients with Headache Response [Headache response was defined as a reduction in headache severity to mild or no pain. Headache response was based on pain intensity as interpreted by the patient using a four-point pain intensity scale.] 2 and 4 Hours Following a Single Treatment of Study Medication [Dihydroergotamine Mesylate Nasal Spray or Placebo]
 |  | N | 2 hours | 4 hours
Study 1 | Dihydroergotamine | 105 | 61% [p value < 0.001] | 70%
 | Mesylate Nasal Spray Placebo | 98 | 23% | 28%
Study 2 | Dihydroergotamine | 103 | 47% | 56% [p value < 0.01]
 | Mesylate Nasal Spray Placebo | 102 | 33% | 35%

Table 2: Studies 3 and 4: Percentage of Patients with Headache Response [Headache response was defined as a reduction in headache severity to mild or no pain. Headache response was evaluated on a five-point scale that included both pain response and restoration of function for “severe” or “incapacitating” pain.] 2 and 4 Hours Following a Single Treatment of Study Medication [Dihydroergotamine Mesylate Nasal Spray or Placebo]
 |  | N | 2 hours | 4 hours
Study 3 | Dihydroergotamine | 50 | 32% | 48% [p value < 0.01]
 | Mesylate Nasal Spray Placebo | 50 | 20% | 22%
Study 4 | Dihydroergotamine | 47 | 30% | 47%
 | Mesylate Nasal Spray Placebo | 50 | 20% | 30%

Comparisons of drug performance based upon results obtained in different clinical trials are never reliable. Because studies are conducted at different times, with different samples of patients, by different investigators, employing different criteria and/or different interpretations of the same criteria, under different conditions (dose, dosing regimen, etc.), quantitative estimates of treatment response and the timing of response may be expected to vary considerably from study to study.

The Kaplan-Meier plots below (Figures 1 & 2) provides an estimate of the probability that a patient will have responded to a single 2 mg dose of Dihydroergotamine Mesylate Nasal Spray as a function of the time elapsed since initiation of treatment.

*The figure shows the probability over time of obtaining a response following treatment with Dihydroergotamine Mesylate Nasal Spray. Headache response was based on pain intensity as interpreted by the patient using a four-point pain intensity scale. Patients not achieving response within 4 hours were censored to 4 hours.

*The figure shows the probability over time of obtaining a response following treatment with Dihydroergotamine Mesylate Nasal Spray. Headache response was evaluated on a five-point scale that confounded pain response and restoration of function for “severe” or “incapacitating” pain. Patients not achieving response within 4 hours were censored to 4 hours.

For patients with migraine-associated nausea, photophobia, and phonophobia at baseline, there was a lower incidence of these symptoms at 2 and 4 hours following administration of Dihydroergotamine Mesylate Nasal Spray compared to placebo.

Patients were not allowed to use additional treatments for eight hours prior to study medication dosing and during the four-hour observation period following study treatment. Following the 4-hour observation period, patients were allowed to use additional treatments. For all studies, the estimated probability of patients using additional treatments for their migraines over the 24 hours following the single 2 mg dose of study treatment is summarized in Figure 3 below.

*Kaplan-Meier plot based on data obtained from all studies with patients not using additional treatments censored to 24 hours. All patients received a single treatment of study medication for their migraine attack. The plot also includes patients who had no response to the initial dose.

Neither age nor sex appear to affect the patient’s response to Dihydroergotamine Mesylate Nasal Spray. While patients with menstrual migraine, migraine with aura, and migraine without aura by medical history were included in the clinical evaluation of Dihydroergotamine Mesylate Nasal Spray, patients were not required to report the specific type of migraine treated with study medication. Thus, neither the effect of menses on migraine nor the presence or the absence of aura were assessed. The racial distribution of patients was insufficient to determine the effect of race on the efficacy of Dihydroergotamine Mesylate Nasal Spray.

INDICATIONS AND USAGE

Dihydroergotamine Mesylate Nasal Spray is indicated for the acute treatment of migraine headaches with or without aura.

Dihydroergotamine Mesylate Nasal Spray is not intended for the prophylactic therapy of migraine or for the management of hemiplegic or basilar migraine.

CONTRAINDICATIONS

There have been a few reports of serious adverse events associated with the coadministration of dihydroergotamine and potent CYP 3A4 inhibitors, such as protease inhibitors and macrolide antibiotics, resulting in vasospasm that led to cerebral ischemia and/or ischemia of the extremities. The use of potent CYP 3A4 inhibitors (ritonavir, nelfinavir, indinavir, erythromycin, clarithromycin, troleandomycin, ketoconazole, itraconazole) with dihydroergotamine is, therefore contraindicated (see WARNINGS, CYP 3A4 Inhibitors).

Dihydroergotamine Mesylate Nasal Spray should not be given to patients with ischemic heart disease (angina pectoris, history of myocardial infarction, or documented silent ischemia) or to patients who have clinical symptoms or findings consistent with coronary artery vasospasm including Prinzmetal’s variant angina (see WARNINGS).

Because Dihydroergotamine Mesylate Nasal Spray may increase blood pressure, it should not be given to patients with uncontrolled hypertension.

Dihydroergotamine Mesylate Nasal Spray, 5-HT1agonists (e.g., sumatriptan), ergotamine-containing or ergot-type medications or methysergide should not be used within 24 hours of each other.

Dihydroergotamine Mesylate Nasal Spray should not be administered to patients with hemiplegic or basilar migraine.

In addition to those conditions mentioned above, Dihydroergotamine Mesylate Nasal Spray is also contraindicated in patients with known peripheral arterial disease, sepsis, following vascular surgery, and severely impaired hepatic or renal function.

Dihydroergotamine Mesylate Nasal Spray is contraindicated in patients who have previously shown hypersensitivity to ergot alkaloids.

Dihydroergotamine mesylate should not be used with peripheral and central vasoconstrictors because the combination may result in additive or synergistic elevation of blood pressure.

WARNINGS

Dihydroergotamine Mesylate Nasal Spray should only be used where a clear diagnosis of migraine headache has been established.

CYP 3A4 Inhibitors (e.g., Macrolide Antibiotics and Protease Inhibitors)

There have been rare reports of serious adverse events in connection with the coadministration of dihydroergotamine and potent CYP 3A4 inhibitors, such as protease inhibitors and macrolide antibiotics, resulting in vasospasm that led to cerebral ischemia and/or and ischemia of the extremities. The use of potent CYP 3A4 inhibitors with dihydroergotamine should therefore be avoided (see CONTRAINDICATIONS). Examples of some of the more potent CYP 3A4 inhibitors include: antifungals ketoconazole and itraconazole, the protease inhibitors ritonavir, nelfinavir, and indinavir, and macrolide antibiotics erythromycin, clarithromycin, and troleandomycin. Other less potent CYP 3A4 inhibitors should be administered with caution. Less potent inhibitors include saquinavir, nefazodone, fluconazole, grapefruit juice, fluoxetine, fluvoxamine, zileuton, and clotrimazole. These lists are not exhaustive, and the prescriber should consider the effects on CYP 3A4 of other agents being considered for concomitant use with dihydroergotamine.

Fibrotic Complications

There have been reports of pleural and retroperitoneal fibrosis in patients following prolonged daily use of injectable dihydroergotamine mesylate. Rarely, prolonged daily use of other ergot alkaloid drugs has been associated with cardiac valvular fibrosis. Rare cases have also been reported in association with the use of injectable dihydroergotamine mesylate; however, in those cases, patients also received drugs known to be associated with cardiac valvular fibrosis.

Administration of Dihydroergotamine Mesylate Nasal Spray, should not exceed the dosing guidelines and should not be used for chronic daily administration (see DOSAGE AND ADMINISTRATION).

Risk of Myocardial Ischemia and/or Infarction and Other Adverse Cardiac Events:

Dihydroergotamine Mesylate Nasal Spray should not be used by patients with documented ischemic or vasospastic coronary artery disease (see CONTRAINDICATIONS). It is strongly recommended that Dihydroergotamine Mesylate Nasal Spray not be given to patients in whom unrecognized coronary artery disease (CAD) is predicted by the presence of risk factors (e.g., hypertension, hypercholesterolemia, smoker, obesity, diabetes, strong family history of CAD, females who are surgically or physiologically postmenopausal, or males who are over 40 years of age) unless a cardiovascular evaluation provides satisfactory clinical evidence that the patient is reasonably free of coronary artery and ischemic myocardial disease or other significant underlying cardiovascular disease. The sensitivity of cardiac diagnostic procedures to detect cardiovascular disease or predisposition to coronary artery vasospasm is modest, at best. If, during the cardiovascular evaluation, the patient’s medical history or electrocardiographic investigations reveal findings indicative of or consistent with coronary artery vasospasm or myocardial ischemia, Dihydroergotamine Mesylate Nasal Spray should not be administered (see CONTRAINDICATIONS).

For patients with risk factors predictive of CAD who are determined to have a satisfactory cardiovascular evaluation, it is strongly recommended that administration of the first dose of Dihydroergotamine Mesylate Nasal Spray take place in the setting of a physician’s office or similar medically staffed and equipped facility unless the patient has previously received dihydroergotamine mesylate. Because cardiac ischemia can occur in the absence of clinical symptoms, consideration should be given to obtaining on the first occasion of use an electrocardiogram (ECG) during the interval immediately following Dihydroergotamine Mesylate Nasal Spray, in these patients with risk factors.

It is recommended that patients who are intermittent long-term users of Dihydroergotamine Mesylate Nasal Spray and who have or acquire risk factors predictive of CAD, as described above, undergo periodic interval cardiovascular evaluation as they continue to use Dihydroergotamine Mesylate Nasal Spray.

The systematic approach described above is currently recommended as a method to identify patients in whom Dihydroergotamine Mesylate Nasal Spray may be used to treat migraine headaches with an acceptable margin of cardiovascular safety.

Cardiac Events and Fatalities

No deaths have been reported in patients using Dihydroergotamine Mesylate Nasal Spray. However, the potential for adverse cardiac events exists. Serious adverse cardiac events, including acute myocardial infarction, life-threatening disturbances of cardiac rhythm, and death have been reported to have occurred following the administration of dihydroergotamine mesylate injection (e.g., D.H.E. 45 Injection). Considering the extent of use of dihydroergotamine mesylate in patients with migraine, the incidence of these events is extremely low.

Drug-Associated Cerebrovascular Events and Fatalities

Cerebral hemorrhage, subarachnoid hemorrhage, stroke, and other cerebrovascular events have been reported in patients treated with D.H.E. 45 Injection; and some have resulted in fatalities. In a number of cases, it appears possible that the cerebrovascular events were primary, the D.H.E. 45 Injection having been administered in the incorrect belief that the symptoms experienced were a consequence of migraine, when they were not. It should be noted that patients with migraine may be at increased risk of certain cerebrovascular events (e.g., stroke, hemorrhage, transient ischemic attack).

Other Vasospasm Related Events

Dihydroergotamine Mesylate Nasal Spray, like other ergot alkaloids, may cause vasospastic reactions other than coronary artery vasospasm. Myocardial and peripheral vascular ischemia have been reported with Dihydroergotamine Mesylate Nasal Spray.

Dihydroergotamine Mesylate Nasal Spray associated vasospastic phenomena may also cause muscle pains, numbness, coldness, pallor, and cyanosis of the digits. In patients with compromised circulation, persistent vasospasm may result in gangrene or death, Dihydroergotamine Mesylate Nasal Spray should be discontinued immediately if signs or symptoms of vasoconstriction develop.

Increase in Blood Pressure

Significant elevation in blood pressure has been reported on rare occasions in patients with and without a history of hypertension treated with Dihydroergotamine Mesylate Nasal Spray and dihydroergotamine mesylate injection. Dihydroergotamine Mesylate Nasal Spray is contraindicated in patients with uncontrolled hypertension (see CONTRAINDICATIONS).

An 18% increase in mean pulmonary artery pressure was seen following dosing with another 5HT1agonist in a study evaluating subjects undergoing cardiac catheterization.

Local Irritation

Approximately 30% of patients using Dihydroergotamine Mesylate Nasal Spray (compared to 9% of placebo patients) have reported irritation in the nose, throat, and/or disturbances in taste. Irritative symptoms include congestion, burning sensation, dryness, paraesthesia, discharge, epistaxis, pain, or soreness. The symptoms were predominantly mild to moderate in severity and transient. In approximately 70% of the above mentioned cases, the symptoms resolved within four hours after dosing with Dihydroergotamine Mesylate Nasal Spray. Examinations of the nose and throat in a small subset (N = 66) of study participants treated for up to 36 months (range 1-36 months) did not reveal any clinically noticeable injury. Other than this limited number of patients, the consequences of extended and repeated use of Dihydroergotamine Mesylate Nasal Spray on the nasal and/or respiratory mucosa have not been systematically evaluated in patients.

Nasal tissue in animals treated with dihydroergotamine mesylate daily at nasal cavity surface area exposures (in mg/mm^2) that were equal to or less than those achieved in humans receiving the maximum recommended daily dose of 0.08 mg/kg/day showed mild mucosal irritation characterized by mucous cell and transitional cell hyperplasia and squamous cell metaplasia. Changes in rat nasal mucosa at 64 weeks were less severe than at 13 weeks. Local effects on respiratory tissue after chronic intranasal dosing in animals have not been evaluated.

Medication Overuse Headache

Overuse of acute migraine drugs (e.g., ergotamines, triptans, opioids, or a combination of these drugs for 10 or more days per month) may lead to exacerbation of headache (i.e., medication overuse headache). Medication overuse headache may present as migraine-like daily headaches or as a marked increase in frequency of migraine attacks. Detoxification of patients including withdrawal of the overused drugs and treatment of withdrawal symptoms (which often includes a transient worsening of headache) may be necessary.

Preterm Labor

Based on the mechanism of action of dihydroergotamine and findings from the published literature, Dihydroergotamine Mesylate Nasal Spray may cause preterm labor. Avoid use of Dihydroergotamine Mesylate Nasal Spray during pregnancy (see PRECAUTIONS).

PRECAUTIONS

General

Dihydroergotamine Mesylate Nasal Spray may cause coronary artery vasospasm; patients who experience signs or symptoms suggestive of angina following its administration should, therefore, be evaluated for the presence of CAD or a predisposition to variant angina before receiving additional doses. Similarly, patients who experience other symptoms or signs suggestive of decreased arterial flow, such as ischemic bowel syndrome or Raynaud’s syndrome following the use of any 5-HT agonist are candidates for further evaluation (see WARNINGS).

Fibrotic Complications:

see WARNINGS, Fibrotic Complications

Information for Patients

The text of a patient information sheet is printed at the end of this insert. To assure safe and effective use of Dihydroergotamine Mesylate Nasal Spray, the information and instructions provided in the patient information sheet should be discussed with patients.

Once the nasal spray applicator has been prepared, it should be discarded (with any remaining drug) after 8 hours.

Patients should be advised to report to the physician immediately any of the following: numbness or tingling in the fingers and toes, muscle pain in the arms and legs, weakness in the legs, pain in the chest, temporary speeding or slowing of the heart rate, swelling, or itching.

Prior to the initial use of the product by a patient, the prescriber should take steps to ensure that the patient understands how to use the product as provided (see Patient Information Sheet and product packaging).

Administration of Dihydroergotamine Mesylate Nasal Spray, should not exceed the dosing guidelines and should not be used for chronic daily administration (see DOSAGE AND ADMINISTRATION).

Drug Interactions

Vasoconstrictors

Dihydroergotamine Mesylate Nasal Spray should not be used with peripheral vasoconstrictors because the combination may cause synergistic elevation of blood pressure.

Sumatriptan

Sumatriptan has been reported to cause coronary artery vasospasm, and its effect could be additive with Dihydroergotamine Mesylate Nasal Spray. Sumatriptan and Dihydroergotamine Mesylate Nasal Spray should not be taken within 24 hours of each other (see CONTRAINDICATIONS).

Beta-Blockers

Although the results of a clinical study did not indicate a safety problem associated with the administration of Dihydroergotamine Mesylate Nasal Spray to subjects already receiving propranolol, there have been reports that propranolol may potentiate the vasoconstrictive action of ergotamine by blocking the vasodilating property of epinephrine.

Nicotine

Nicotine may provoke vasoconstriction in some patients, predisposing to a greater ischemic response to ergot therapy.

CYP 3A4 Inhibitors (e.g., Macrolide Antibiotics and Protease Inhibitors)

See CONTRAINDICATIONSand WARNINGS.

SSRI’s

Weakness, hyperreflexia, and incoordination have been reported rarely when 5HT1agonists have been coadministered with SSRI’s (e.g., fluoxetine, fluvoxamine, paroxetine, sertraline). There have been no reported cases from spontaneous reports of drug interaction between SSRI’s and Dihydroergotamine Mesylate Nasal Spray or D.H.E. 45.

Oral Contraceptives

The effect of oral contraceptives on the pharmacokinetics of Dihydroergotamine Mesylate Nasal Spray has not been studied.

Carcinogenesis, Mutagenesis, Impairment of Fertility

Carcinogenesis

In a 2-year mouse carcinogenicity study, subcutaneous administration of dihydroergotamine mesylate (0, 0.5, 1.5 or 5 mg/kg/day) resulted in an increased incidence of fibrosarcoma at the injection sites in males and females at the high dose.

In a 2-year rat carcinogenicity study, intranasal administration of dihydroergotamine mesylate (0, 0.4, 0.8 or 1.6 mg/day for 13 weeks, followed by 0, 0.08, 0.24 or 0.8 mg/day for the remainder of the study) did not result in an increase in tumors.

Mutagenesis

Dihydroergotamine mesylate was clastogenic in two in vitro chromosomal aberration assays, the V79 Chinese hamster cell assay with metabolic activation and the cultured human peripheral blood lymphocyte assay. There was no evidence of mutagenic potential when dihydroergotamine mesylate was tested in the presence or absence of metabolic activation in two gene mutation assays (the Ames test and the in vitro mammalian Chinese hamster V79/HGPRT assay) and in an assay for DNA damage (the rat hepatocyte unscheduled DNA synthesis test). Dihydroergotamine was not clastogenic in the in vivo mouse and hamster micronucleus tests.

Impairment of Fertility

Intranasal administration of dihydroergotamine to rats at doses up to 1.6 mg/day was not associated with adverse effects on fertility.

Pregnancy

Risk Summary

Available data from published literature indicate an increased risk of preterm delivery with Dihydroergotamine Mesylate Nasal Spray use during pregnancy. Avoid use of Dihydroergotamine Mesylate Nasal Spray during pregnancy (see WARNINGS). Data collected over decades have shown no increased risk of major birth defects or miscarriage with the use of dihydroergotamine mesylate during pregnancy .

In animal reproduction studies, adverse effects on development were observed following intranasal administration of dihydroergotamine mesylate during pregnancy (decreased fetal body weight and/or skeletal ossification) in rats and rabbits or during pregnancy and lactation in rats (decreased body weight and impaired reproductive function in the offspring) at doses that were not associated with maternal toxicity (see Data).

The estimated rate of major birth defects (2.2% to 2.9%) and miscarriage (17%) among deliveries to women with migraine are similar to rates reported in women without migraine. All pregnancies have a background risk of birth defect, loss, or other adverse outcomes. In the U.S. general population, the estimated background risk of major birth defects and miscarriages in clinically recognized pregnancies is 2% to 4% and 15% to 20%, respectively.

Data

Animal Data

Intranasal administration of dihydroergotamine mesylate to pregnant rats throughout the period of organogenesis resulted in decreased fetal body weight and/or skeletal ossification at doses of 0.16 mg/day and greater. A no-effect level for adverse effects on embryofetal development was not identified in rats. Intranasal administration of dihydroergotamine mesylate to pregnant rabbits throughout organogenesis resulted in decreased skeletal ossification at 3.6 mg/day. The no-effect dose for adverse effects on embryofetal development in rabbits was 1.2 mg/day.

Intranasal administration of dihydroergotamine mesylate to female rats throughout pregnancy and lactation resulted in decreased body weight and impaired reproductive function (decreased mating indices) in the offspring at doses of 0.16 mg/day or greater. A no-effect dose for adverse effects on pre- and postnatal development in rats was not established. Effects on offspring development occurred at doses below those that produced evidence of maternal toxicity in these studies. Dihydroergotamine-induced intrauterine growth retardation has been attributed to reduced uteroplacental blood flow resulting from prolonged vasoconstriction of the uterine vessels and/or increased myometrial tone.

Nursing Mothers

There are no data on the presence of dihydroergotamine in human milk; however, ergotamine, a related drug, is present in human milk. There are reports of diarrhea, vomiting, weak pulse, and unstable blood pressure in breastfed infants exposed to ergotamine. Dihydroergotamine Mesylate Nasal Spray may reduce milk supply because it may decrease prolactin levels. Because of the potential for reduced milk supply and serious adverse events in the breastfed infant, including diarrhea, vomiting, weak pulse, and unstable blood pressure, advise patients not to breastfeed during treatment with Dihydroergotamine Mesylate Nasal Spray and for 3 days after the last dose. Breast milk supply during this time should be pumped and discarded.

Pediatric Use

Safety and effectiveness in pediatric patients have not been established.

Use in the Elderly

There is no information about the safety and effectiveness of Dihydroergotamine Mesylate Nasal Spray in this population because patients over age 65 were excluded from the controlled clinical trials.

ADVERSE REACTIONS

During clinical studies and the foreign postmarketing experience with Dihydroergotamine Mesylate Nasal Spray there have been no fatalities due to cardiac events.

Serious cardiac events, including some that have been fatal, have occurred following use of the parenteral form of dihydroergotamine mesylate (D.H.E. 45 Injection), but are extremely rare. Events reported have included coronary artery vasospasm, transient myocardial ischemia, myocardial infarction, ventricular tachycardia, and ventricular fibrillation (see CONTRAINDICATIONS, WARNINGS, and PRECAUTIONS).

Fibrotic complications have been reported in association with long term use of injectable dihydroergotamine mesylate (see WARNINGS, Fibrotic Complications).

Incidence in Controlled Clinical Trials

Of the 1,796 patients and subjects treated with Dihydroergotamine Mesylate Nasal Spray doses 2 mg or less in U.S. and foreign clinical studies, 26 (1.4%) discontinued because of adverse events. The adverse events associated with discontinuation were, in decreasing order of frequency: rhinitis 13, dizziness 2, facial edema 2, and one each due to cold sweats, accidental trauma, depression, elective surgery, somnolence, allergy, vomiting, hypotension, and paraesthesia.

The most commonly reported adverse events associated with the use of Dihydroergotamine Mesylate Nasal Spray during placebo-controlled, double-blind studies for the treatment of migraine headache and not reported at an equal incidence by placebo-treated patients were rhinitis, altered sense of taste, application site reactions, dizziness, nausea, and vomiting. The events cited reflect experience gained under closely monitored conditions of clinical trials in a highly selected patient population. In actual clinical practice or in other clinical trials, these frequency estimates may not apply, as the conditions of use, reporting behavior, and the kinds of patients treated may differ.

Dihydroergotamine Mesylate Nasal Spray was generally well tolerated. In most instances these events were transient and self-limited and did not result in patient discontinuation from a study. The following table summarizes the incidence rates of adverse events reported by at least 1% of patients who received Dihydroergotamine Mesylate Nasal Spray for the treatment of migraine headaches during placebo-controlled, double-blind clinical studies and were more frequent than in those patients receiving placebo.

Table 3: Adverse Reactions Reported by at least 1% of the Dihydroergotamine Mesylate Nasal Spray Treated Patients and Occurred More Frequently than in the Placebo-Group in the Migraine Placebo-Controlled Trials
 | Dihydroergotamine Mesylate Nasal Spray N=597 | Placebo N=631
Respiratory System
Rhinitis | 26% | 7%
Pharyngitis | 3% | 1%
Sinusitis | 1% | 1%
Gastrointestinal System
Nausea | 10% | 4%
Vomiting | 4% | 1%
Diarrhea | 2% | <1%
Special Senses, Other
Altered Sense of Taste | 8% | 1%
Application Site
Application Site Reaction | 6% | 2%
Central and Peripheral Nervous System
Dizziness | 4% | 2%
Somnolence | 3% | 2%
Paraesthesia | 2% | 2%
Body as a Whole, General
Hot Flashes | 1% | <1%
Fatigue | 1% | 1%
Asthenia | 1% | 0%
Autonomic Nervous System
Mouth Dry | 1% | 1%
Musculoskeletal System
Stiffness | 1% | <1%

Other Adverse Events During Clinical Trials

In the paragraphs that follow, the frequencies of less commonly reported adverse clinical events are presented. Because the reports include events observed in open and uncontrolled studies, the role of Dihydroergotamine Mesylate Nasal Spray in their causation cannot be reliably determined. Furthermore, variability associated with adverse event reporting, the terminology used to describe adverse events, etc., limit the value of the quantitative frequency estimates provided. Event frequencies are calculated as the number of patients who used Dihydroergotamine Mesylate Nasal Spray in placebo-controlled trials and reported an event divided by the total number of patients (n=1796) exposed to Dihydroergotamine Mesylate Nasal Spray. All reported events are included except those already listed in the previous table, those too general to be informative, and those not reasonably associated with the use of the drug. Events are further classified within body system categories and enumerated in order of decreasing frequency using the following definitions: frequent adverse events are defined as those occurring in at least 1/100 patients; infrequent adverse events are those occurring in 1/100 to 1/1,000 patients; and rare adverse events are those occurring in fewer than 1/1,000 patients.

Skin and Appendages:Infrequent: petechia, pruritus, rash, cold clammy skin; Rare: papular rash, urticaria, herpes simplex.

Musculoskeletal:Infrequent: cramps, myalgia, muscular weakness, dystonia; Rare: arthralgia, involuntary muscle contractions, rigidity.

Central and Peripheral Nervous System:Infrequent: confusion, tremor, hypoesthesia, vertigo; Rare: speech disorder, hyperkinesia, stupor, abnormal gait, aggravated migraine.

Autonomic Nervous System: Infrequent:increased sweating.

Special Senses:Infrequent: sense of smell altered, photophobia, conjunctivitis, abnormal lacrimation, abnormal vision, tinnitus, earache; Rare:eye pain.

Psychiatric:Infrequent: nervousness, euphoria, insomnia, concentration impaired; Rare: anxiety, anorexia, depression.

Gastrointestinal:Infrequent: abdominal pain, dyspepsia, dysphagia, hiccup; Rare: increased salivation, esophagospasm.

Cardiovascular:Infrequent: edema, palpitation, tachycardia; Rare:hypotension, peripheral ischemia, angina.

Respiratory System:Infrequent: dyspnea, upper respiratory tract infections; Rare: bronchospasm, bronchitis, pleural pain, epistaxis.

Urinary System:Infrequent: increased frequency of micturition, cystitis.

Reproductive, Female:Rare: pelvic inflammation, vaginitis.

Body as a Whole -General: Infrequent:feeling cold, malaise, rigors, fever, periorbital edema; Rare: flu-like symptoms, shock, loss of voice, yawning.

Application Site:Infrequent: local anesthesia.

Post-introduction Reports

Voluntary reports of adverse events temporally associated with dihydroergotamine products used in the management of migraine that have been received since the introduction of the injectable formulation are included in this section save for those already listed above. Because of their source (open and uncontrolled clinical use), whether or not events reported in association with the use of dihydroergotamine are causally related to it cannot be determined. There have been reports of pleural and retroperitoneal fibrosis in patients following prolonged daily use of injectable dihydroergotamine mesylate. Dihydroergotamine Mesylate Nasal Spray is not recommended for prolonged daily use (see DOSAGE AND ADMINISTRATION).

To report SUSPECTED ADVERSE REACTIONS, contact Bausch Health US, LLC at 1-800-321-4576 or FDA at 1-800-FDA-1088 or www.fda.gov/medwatch.

DRUG ABUSE AND DEPENDENCE

Currently available data have not demonstrated drug abuse or psychological dependence with dihydroergotamine. However, cases of drug abuse and psychological dependence in patients on other forms of ergot therapy have been reported. Thus, due to the chronicity of vascular headaches, it is imperative that patients be advised not to exceed recommended dosages.

OVERDOSAGE

To date, there have been no reports of acute overdosage with this drug. Due to the risk of vascular spasm, exceeding the recommended dosages of Dihydroergotamine Mesylate Nasal Spray is to be avoided.

Excessive doses of dihydroergotamine may result in peripheral signs and symptoms of ergotism. Treatment includes discontinuance of the drug, local application of warmth to the affected area, the administration of vasodilators, and nursing care to prevent tissue damage.

In general, the symptoms of an acute Dihydroergotamine Mesylate Nasal Spray overdose are similar to those of an ergotamine overdose, although there is less pronounced nausea and vomiting with Dihydroergotamine Mesylate Nasal Spray. The symptoms of an ergotamine overdose include the following: numbness, tingling, pain, and cyanosis of the extremities associated with diminished or absent peripheral pulses; respiratory depression; an increase and/or decrease in blood pressure, usually in that order; confusion, delirium, convulsions, and coma; and/or some degree of nausea, vomiting, and abdominal pain.

In laboratory animals, significant lethality occurs when dihydroergotamine is given at I.V. doses of 44 mg/kg in mice, 130 mg/kg in rats, and 37 mg/kg in rabbits.

Up-to-date information about the treatment of overdosage can often be obtained from a certified Regional Poison Control Center. Telephone numbers of certified Poison Control Centers are listed in the Physicians’ Desk Reference (PDR).*

DOSAGE AND ADMINISTRATION

The solution used in Dihydroergotamine Mesylate Nasal Spray (4 mg/mL) is intended for intranasal use and must not be injected.

In clinical trials, Dihydroergotamine Mesylate Nasal Spray has been effective for the acute treatment of migraine headaches with or without aura. One spray (0.5 mg) of Dihydroergotamine Mesylate Nasal Spray should be administered in each nostril. Fifteen minutes later, an additional one spray (0.5 mg) of Dihydroergotamine Mesylate Nasal Spray should be administered in each nostril, for a total dosage of four sprays (2 mg) of Dihydroergotamine Mesylate Nasal Spray. Studies have shown no additional benefit from acute doses greater than 2 mg for a single migraine administration. The safety of doses greater than 3 mg in a 24-hour period and 4 mg in a 7‑day period has not been established.

Dihydroergotamine Mesylate Nasal Spray, should not be used for chronic daily administration.

Prior to administration, the pump must be primed (i.e., squeeze 4 times) before use (see administration instructions). Once the nasal spray applicator has been prepared, it should be discarded (with any remaining drug in opened vial) after 8 hours.

Prior to administration, the pump must be primed (i.e., squeeze 4 times) before use (see administration instructions).

Once the nasal spray applicator has been prepared, it should be discarded (with any remaining drug in opened vial after 8 hours).

HOW SUPPLIED

Dihydroergotamine Mesylate Nasal Spray is available (as a clear, colorless to light yellow aqueous solution) in 3.5 mL amber glass vials containing 4 mg of dihydroergotamine mesylate.

Dihydroergotamine Mesylate Nasal Spray is provided as a package of 8 units, administration instruction sheet, and one package insert. Each unit consists of one vial and one sprayer (NDC 68682-357-10).

STORAGE AND HANDLING

Store below 25°C (77°F). Do not refrigerate or freeze.

*Trademark of PDR Network, LLC

Distributed by:

Oceanside Pharmaceuticals, a division of

Bausch Health US, LLC

Bridgewater, NJ 08807 USA

Manufactured by:

Mipharm, S.p.A.

Milano, Italy

© 2022 Bausch Health Companies Inc. or its affiliates

Rev. 09/2022

9606502

Patient Information

Information for the Patient

Dihydroergotamine Mesylate Nasal Spray

The solution used in Dihydroergotamine Mesylate Nasal Spray (4 mg/mL) is intended for intranasal use and must not be injected.

Please read this information carefully before using your Dihydroergotamine Mesylate Nasal Spray for the first time. Keep this information handy for future reference. This leaflet does not contain all of the information on Dihydroergotamine Mesylate Nasal Spray. Your pharmacist and/or health care provider can provide more detailed information.

Dihydroergotamine Mesylate Nasal Spray has been evaluated in a limited number of patients long term (e.g., 1 year or longer).

Purpose of your Medication

Dihydroergotamine Mesylate Nasal Spray is intended to treat an active migraine headache. Do not try to use it to prevent a headache if you have no symptoms. Do not use it to treat common tension headache or a headache that is not at all typical of your usual migraine headache. Administration of Dihydroergotamine Mesylate Nasal Spray, should not exceed the dosing guidelines and should not be used for chronic daily administration. There have been reports of fibrosis (stiffening) in the lung or kidney areas in patients following prolonged daily use of injectable dihydroergotamine mesylate. Rarely, prolonged daily use of other ergot alkaloid drugs (the class of drugs to which Dihydroergotamine Mesylate Nasal Spray belongs) has been associated with heart valvular fibrosis. Rare cases have also been reported in association with the use of injectable dihydroergotamine mesylate; however, in those cases, patients also received drugs known to be associated with heart valvular fibrosis.

Do not use Dihydroergotamine Mesylate Nasal Spray if you:

- have any disease affecting your heart, arteries, or circulation.
- are taking certain anti-HIV medications (protease inhibitors).
- are taking a macrolide antibiotic such as troleandomycin, clarithromycin or erythromycin.

Important questions to consider before using Dihydroergotamine Mesylate Nasal Spray

Please answer the following questions before you use your Dihydroergotamine Mesylate Nasal Spray. If you answer YES to any of these questions or are unsure of the answer, you should talk to your doctor before using Dihydroergotamine Mesylate Nasal Spray.

- Do you have high blood pressure?
- Do you have chest pain, shortness of breath, heart disease, or have you had any surgery on your heart arteries?
- Do you have risk factors for heart disease (such as high blood pressure, high cholesterol, obesity, diabetes, smoking, strong family history of heart disease, or are you postmenopausal or a male over 40)?
- Do you have any problems with blood circulation in your arms or legs, fingers, or toes?
- Are you pregnant? Do you think you might be pregnant? Are you trying to become pregnant? Are you sexually active and not using birth control?
- Dihydroergotamine Mesylate Nasal Spray may cause preterm labor. Dihydroergotamine Mesylate Nasal Spray should be avoided during pregnancy. Talk to your healthcare provider right away if you are pregnant or want to become pregnant.
- Are you breastfeeding?
- Dihydroergotamine Mesylate Nasal Spray may reduce breast milk supply and pass into your breast milk. Dihydroergotamine Mesylate Nasal Spray may be harmful to your baby. Do not breastfeed your baby while taking Dihydroergotamine Mesylate Nasal Spray and for 3 days after you use Dihydroergotamine Mesylate Nasal Spray. Talk with your healthcare provider about the best way to feed your baby if you take Dihydroergotamine Mesylate Nasal Spray.
- Have you ever had to stop taking this or any other medication because of an allergy or bad reaction?
- Are you taking any other migraine medications, erythromycin or other antibiotics, or medications for blood pressure prescribed by your doctor, or other medicines obtained from your drugstore without a doctor’s prescription?
- Do you smoke?
- Have you had, or do you have, any disease of the liver or kidney?
- Is this headache different from your usual migraine attacks?
- Are you using Dihydroergotamine Mesylate Nasal Spray or other dihydroergotamine mesylate containing drugs on a daily basis?
- Are you taking a protease inhibitor for HIV therapy?
- Are you taking a macrolide class of antibiotic?

Serious or potentially life-threatening reductions in blood flow to the brain or extremities have been reported rarely due to interactions between Dihydroergotamine Mesylate Nasal Spray and protease inhibitors or macrolide antibiotics.

REMEMBER TO TELL YOUR DOCTOR IF YOU HAVE ANSWERED YES TO ANY OF THESE QUESTIONS BEFORE YOU USE DIHYDROERGOTAMINE MESYLATE NASAL SPRAY.

Side Effects To Watch Out For

In clinical trials, most migraine patients have used Dihydroergotamine Mesylate Nasal Spray without serious side effects. You may experience some nasal congestion or irritation, altered sense of taste, sore throat, nausea, vomiting, dizziness, and fatigue after using Dihydroergotamine Mesylate Nasal Spray. These side effects are temporary and usually do not require you to stop using Dihydroergotamine Mesylate Nasal Spray. Although the following reactions rarely occur, they can be serious and should be reported to your physician immediately:

- Numbness or tingling in your fingers and toes
- Pain, tightness, or discomfort in your chest
- Muscle pain or cramps in your arms and legs
- Weakness in your legs
- Temporary speeding or slowing of your heart rate
- Swelling or itching

Dosing Information

- Each vial contains one complete dose of Dihydroergotamine Mesylate Nasal Spray, which is 1 spray in each nostril followed in 15 minutes by an additional spray in each nostril, for a total of 4 sprays.
- Studies have shown no benefit from acute doses greater than 2 mg (4 sprays) for a single administration. The safety of doses greater than 3 mg in a 24 hour period has not been established.
- The safety of doses greater than 4 mg in a 7-day period has not been established.
- Dihydroergotamine Mesylate Nasal Spray, should not be used for chronic daily administration.

Learn what to do in case of an Overdose

If you have used more medication than you have been instructed, contact your doctor, hospital emergency department, or nearest poison control center immediately.

How to use the Dihydroergotamine Mesylate Nasal Spray

1. Use available training materials.
2. Read and follow the instructions in the administration instructions which are provided with the Dihydroergotamine Mesylate Nasal Spray package before attempting to use the product.
3. If there are any questions concerning the use of your Dihydroergotamine Mesylate Nasal Spray, ask your doctor or pharmacist, or contact Bausch Health US, LLC at 1-800-321-4576.
4. Check the contents of the package:
5. 8 Nasal Spray Vials
6. 8 Nasal Sprayers
7. Administration Instructions
8. Package Insert
9. Assemble the sprayer:
  Assemble your nasal sprayer only when you are ready to use it.
10. Lift tab to bend back blue cover. In one piece, completely remove the blue cover and metal seal in a circular motion. Keeping the vial upright, remove rubber stopper. Set vial aside.
11. Remove plastic cover from the bottom of pump unit. Insert spray pump into vial and turn clockwise until securely fastened.
12. Using the sprayer:
13. Remove cap from spray unit. Holding the vial upright, point nasal sprayer away from face and pump 4 times before using. DO NOT PUMP MORE THAN 4 TIMES. (Although some medication will spray out, there is enough medication in each vial to allow you to prepare your nasal spray pump properly and still receive a full treatment of Dihydroergotamine Mesylate Nasal Spray.)
14. Spray once into each nostril. Do not tilt head back or sniff through your nose while spraying or immediately after.Wait 15 minutes. Spray once again into each nostril.
15. After completing these instructions:
16. Carefully dispose of the nasal spray pump with the vial.

Important Notes:

- Once a Dihydroergotamine Mesylate Nasal Spray vial has been opened, it must be thrown away after 8 hours.

Storing Dihydroergotamine Mesylate Nasal Spray

- Keep medication in a safe place away from children
- Keep Dihydroergotamine Mesylate Nasal Spray away from heat and light.
- Do not expose Dihydroergotamine Mesylate Nasal Spray to temperatures over 77°F.
- Never refrigerate or freeze Dihydroergotamine Mesylate Nasal Spray.
- Do not keep an opened Dihydroergotamine Mesylate Nasal Spray vial for more than 8 hours.
- Check the expiration date printed on the vial containing medication. If the expiration date has passed, do not use it.

Answers to patients’ questions about Dihydroergotamine Mesylate Nasal Spray

What if I need help in using my Dihydroergotamine Mesylate Nasal Spray?

If you have any questions or if you need help in opening, putting together, or using Dihydroergotamine Mesylate Nasal Spray, speak to your doctor or pharmacist, or contact Bausch Health US, LLC at 1-800-321-4576.

How much medication should I use and how often?

Each vial contains one complete dose of Dihydroergotamine Mesylate Nasal Spray, which is 1 spray in each nostril, followed by an additional spray in each nostril 15 minutes later for a total of 4 sprays. Do not use more than this amount unless instructed to do so by your doctor. Dihydroergotamine Mesylate Nasal Spray is not intended for chronic daily use.

Why do I have to prime or pump the Nasal Sprayer 4 times before using? Am I wasting the medication?

You have to prime the Nasal Sprayer 4 times to make sure that you get the proper amount of medication when you use it. Although you will see some medication spray out, there is still enough medication in each vial to allow you to prepare your sprayer properly and still receive a full dose of Dihydroergotamine Mesylate Nasal Spray.

Can I assemble the medication vial and the Nasal Sprayer so it is ready before I need to use it?

No. The brown (amber) glass vial containing your medication must remain unopened until you are ready to use it. It may not be fully effective if opened and not used within 8 hours.

Can I reuse my Dihydroergotamine Mesylate Nasal Sprayer?

No. After completing the full dose, you must carefully dispose of your Dihydroergotamine Mesylate Nasal Sprayer and the opened vial. You should use a new unit for your next migraine attack. Each Unit contains a new Nasal Sprayer, and a vial of Dihydroergotamine Mesylate Nasal Spray medication.

Can I use Dihydroergotamine Mesylate Nasal Spray if I have a stuffy nose, cold, or allergies?

Yes. Dihydroergotamine Mesylate Nasal Spray can be used if you have a stuffy nose, cold, or allergies. However, if you are taking any medications for your cold, or allergies, even those you can buy without a doctor’s prescription, speak with your doctor before using Dihydroergotamine Mesylate Nasal Spray.

Do I need to sniff the medication when I spray it in my nostril?

No, you should not sniff because Dihydroergotamine Mesylate Nasal Spray should remain in the nose so that it can be absorbed into the bloodstream through the lining of the nose.

If you have any other unanswered questions about Dihydroergotamine Mesylate Nasal Spray, consult your doctor or pharmacist.

Distributed by:

Oceanside Pharmaceuticals, a division of

Bausch Health US, LLC

Bridgewater, NJ 08807 USA

Manufactured by:

Mipharm, S.p.A.

Milano, Italy

© 2022 Bausch Health Companies Inc. or its affiliates

Rev. 09/2022

9606502

PRINCIPAL DISPLAY PANEL - 4 mg/mL Vial Carton

NDC68682-357-10
Rx only

Dihydroergotamine Mesylate
NASAL SPRAY

This Kit Contains:

- 8 Dihydroergotamine Mesylate Vials
- 8 Dihydroergotamine Mesylate Nasal Sprayers
- Administration Instructions
- Package Insert

FOR NASAL USE ONLY-NOT FOR INJECTION

4mg/mL (1 mL/Vial)

9613302